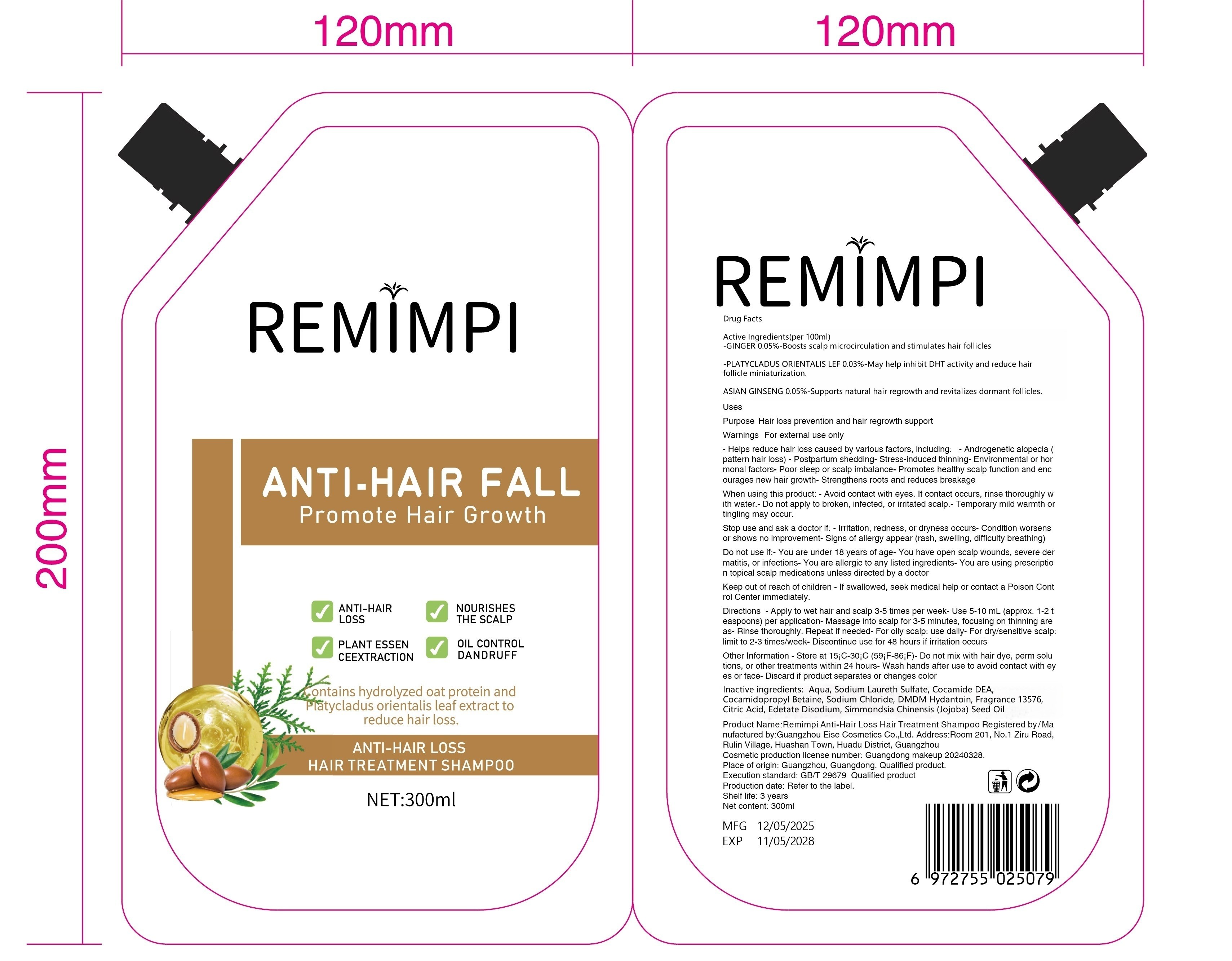 DRUG LABEL: hairtreatmentshampoo
NDC: 84778-074 | Form: LIQUID
Manufacturer: Guangzhou Yixin Cross-border E-commerce Co., Ltd.
Category: otc | Type: HUMAN OTC DRUG LABEL
Date: 20250601

ACTIVE INGREDIENTS: PLATYCLADUS ORIENTALIS LEAF 0.03 g/100 g
INACTIVE INGREDIENTS: AQUA; FRAGRANCE 13576; GINGER 0.05 g/100 g; COCAMIDE DEA; COCAMIDOPROPYL BETAINE; SODIUM LAURETH SULFATE; CITRIC ACID; ASIAN GINSENG 0.05 g/100 g; SODIUM CHLORIDE; EDETATE DISODIUM; DMDM HYDANTOIN; SIMMONDSIA CHINENSIS (JOJOBA) SEED OIL

Active ingredients

GINGER 0.05% – Boosts scalp microcirculation and stimulates hair follicles.

PLATYCLADUS ORIENTALIS LEAF 0.03% – May help inhibit DHT activity and reduce hair follicle miniaturization.
ASIAN GINSENG 0.05% – Supports natural hair regrowth and revitalizes dormant follicles.

Purpose

Hair loss prevention and hair regrowth support

Uses

Helps reduce hair loss caused by various factors, including:
– Androgenetic alopecia (pattern hair loss)
– Postpartum hair shedding
– Stress-induced hair thinning
– Environmental damage
– Poor sleep or hormonal imbalance

Supports healthy scalp function and promotes natural hair regrowth.
Strengthens hair from the roots to reduce breakage and shedding.

Warnings

For external use only.

When using this product:
– Avoid contact with eyes. If contact occurs, rinse thoroughly with water.
– Do not apply to broken or irritated scalp.

Stop use and ask a doctor if:
– Irritation, redness, or excessive dryness occurs.
– Condition worsens or does not improve after regular use.

Keep out of reach of children.
– If swallowed, get medical help or contact a Poison Control Center right away.

Dosage and administration

Frequency: Apply to wet scalp 3-5 times weekly. Adjust based on hair type:

Oily scalp: Up to daily use.

Dry/sensitive scalp: Reduce to 2-3 times weekly.

Amount: Use 5-10 mL (approximately 1-2 teaspoonfuls) per application.

Steps:

Wet hair and scalp thoroughly with warm water.

Gently massage shampoo into scalp for 3-5 minutes, focusing on thinning areas.

Rinse completely. For deeper cleansing, repeat application once.

Follow with conditioner if needed.

Note: Allow 48 hours between uses if scalp sensitivity occurs.

Do NOT use this product if:

You are allergic to any ingredient listed under "Active Ingredients" or "Inactive Ingredients".

You are under 18 years old (safety not established in pediatric populations).

Your scalp has open wounds, burns, infections (e.g., psoriasis, severe dandruff), or active inflammation.

You are using prescription topical medications (e.g., corticosteroids, retinoids) unless directed by a doctor.

When using section

Precautions during use:

Avoid mixing with other hair treatments (e.g., chemical dyes, perms) unless spaced by 24 hours.

Store at room temperature (15°C–30°C). Discard if product separates or changes color.

Wash hands immediately after application to prevent accidental transfer to face or eyes.

Temporary mild scalp warmth or tingling may occur due to active botanical extracts (e.g., ginger). If persistent, discontinue use.

stop use

Discontinue use and consult a healthcare provider if:

Scalp irritation, itching, or flaking persists for >72 hours after stopping the product.

You develop a rash, hives, swelling, or difficulty breathing (signs of allergic reaction).

Hair loss increases unexpectedly or new patches of hair loss appear.

You experience systemic symptoms (e.g., dizziness, nausea) possibly linked to accidental ingestion.

Keep out of reach of children.

Inactive ingredients

Aqua , Sodium Laureth Sulfate, Cocamide DEA, Cocamidopropyl Betaine, Sodium Chloride, DMDM Hydantoin,FRAGRANCE 13576 , Citric Acid, EDETATE DISODIUM, Simmondsia Chinensis (Jojoba) Seed Oil